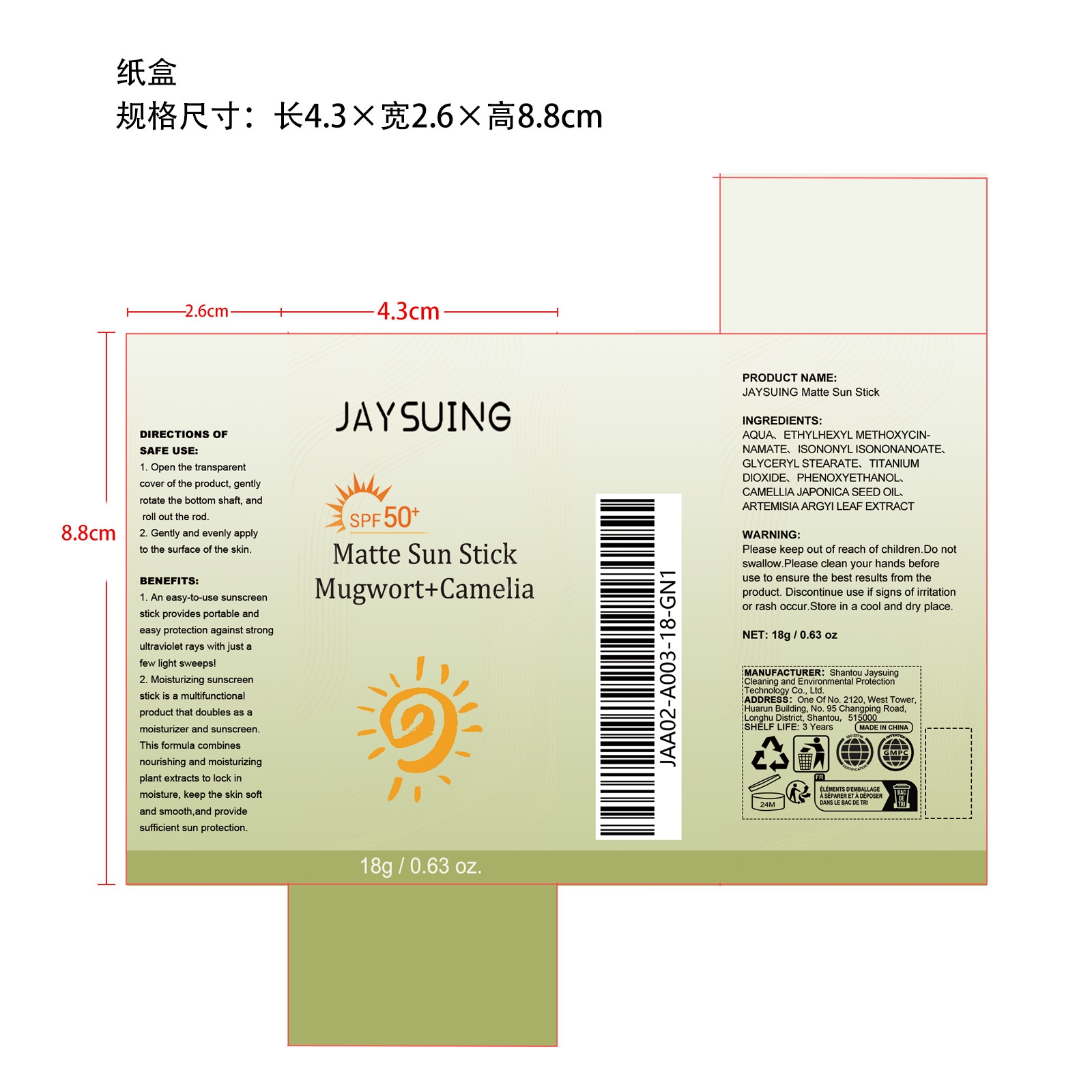 DRUG LABEL: JAYSUING Matte Sun Stick
NDC: 85060-009 | Form: CREAM
Manufacturer: Shantou Jaysuing Cleaning and Environmental Protection Technology Co., Ltd.
Category: otc | Type: HUMAN OTC DRUG LABEL
Date: 20251208

ACTIVE INGREDIENTS: CAMELLIA JAPONICA SEED OIL 0.0036 mg/18 mg; ARTEMISIA ARGYI LEAF 0.0036 mg/18 mg
INACTIVE INGREDIENTS: GLYCERYL STEARATE 0.27 mg/18 mg; TITANIUM DIOXIDE 0.18 mg/18 mg; ETHYLHEXYL METHOXYCINNAMATE 0.9 mg/18 mg; ISONONYL ISONONANOATE 0.72 mg/18 mg; PHENOXYETHANOL 0.054 mg/18 mg; AQUA 15.8688 mg/18 mg

ACTIVE INGREDIENT

CAMELLIA JAPONICA SEED OIL、ARTEMISIA ARGYI LEAF EXTRACT

PURPOSE

1. An easy-to-use sunscreen stick provides portable and easy protection against strong ultraviolet rays with just a few light sweeps!

2. Moisturizing sunscreen stick is a multifunctional product that doubles as a moisturizer and sunscreen. This formula combines nourishing and moisturizing plant extracts to lock in moisture, keep the skin soft and smooth,and provide sufficient sun protection.

WHEN USING

1. Open the transparent cover of the product, gently rotate the bottom shaft, and roll out the rod.

2. Gently and evenly apply to the surface of the skin.

WARNINGS

Please keep out of reach of children. Do not swallow.Please clean your hands before use to ensure the best results from the product. Discontinue use if signs of irritation or rash occur. Store in a cool and dry place.

DO NOT USE

Discontinue use if signs of irritation or rash occur.

STOP USE

Discontinue use if signs of irritation or rash occur.

KEEP OUT OF REACH OF CHILDREN

Please keep out of reach of children. Do not swallow.

STORAGE AND HANDLING

Store in a cool and dry place.

INACTIVE INGREDIENT

AQUA、ETHYLHEXYL METHOXYCINNAMATE、ISONONYL ISONONANOATE、GLYCERYL STEARATE、TITANIUM DIOXIDE、

PHENOXYETHANOL

DOSAGE AND ADMINISTRATION

1. Open the transparent cover of the product, gently rotate the bottom shaft, and roll out the rod.

2. Gently and evenly apply to the surface of the skin.

INDICATIONS AND USAGE

1. Open the transparent cover of the product, gently rotate the bottom shaft, and roll out the rod.

2. Gently and evenly apply to the surface of the skin.